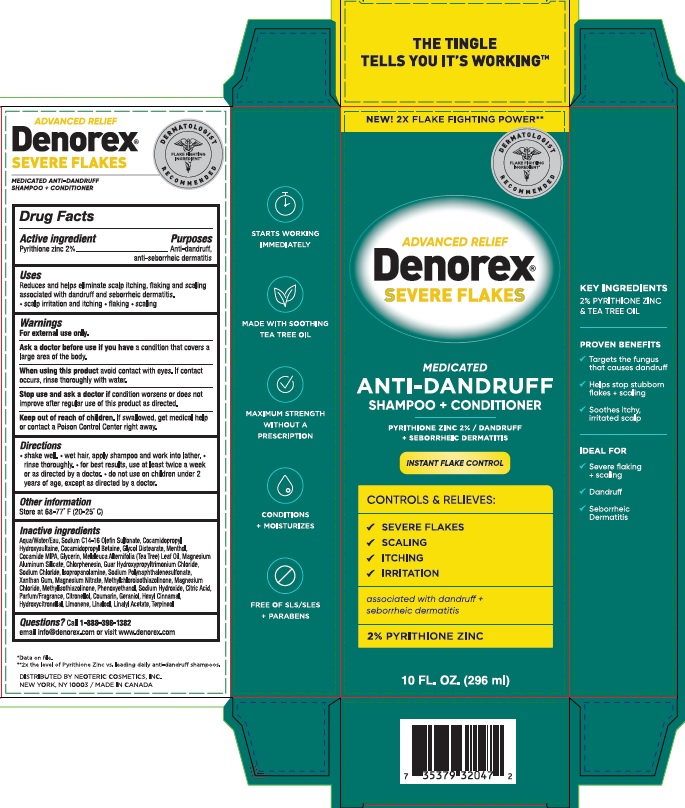 DRUG LABEL: Denorex Severe Flakes
NDC: 62673-176 | Form: SHAMPOO
Manufacturer: Neoteric Cosmetics, Inc.
Category: otc | Type: HUMAN OTC DRUG LABEL
Date: 20251021

ACTIVE INGREDIENTS: ZINC PYRITHIONE 0.02 g/1 mL
INACTIVE INGREDIENTS: COCAMIDOPROPYL BETAINE; MELALEUCA ALTERNIFOLIA (TEA TREE) LEAF OIL; XANTHAN GUM; MAGNESIUM CHLORIDE; METHYLISOTHIAZOLINONE; HEXYL CINNAMAL; PHENOXYETHANOL; CITRONELLOL; GUAR HYDROXYPROPYLTRIMONIUM CHLORIDE; WATER; COCAMIDOPROPYL HYDROXYSULTAINE; FORMALDEHYDE/SODIUM NAPHTHALENESULFONATE COPOLYMER (3000 MW); MAGNESIUM NITRATE; HYDROXYCITRONELLAL; LINALOOL; LINALYL ACETATE; MAGNESIUM ALUMINUM SILICATE; CHLORPHENESIN; SODIUM C14-16 OLEFIN SULFONATE; MENTHOL; SODIUM CHLORIDE; METHYLCHLOROISOTHIAZOLINONE; CITRIC ACID; GLYCOL DISTEARATE; COCAMIDE MIPA; GLYCERIN; ISOPROPANOLAMINE; SODIUM HYDROXIDE; LIMONENE, (+)-; TERPINEOL; COUMARIN; GERANIOL

Denorex Severe Flakes Medicated Anti-Dandruff Shampoo + Conditioner (2% Pyrithione Zinc)

Active ingredient

Pyrithione zinc 2%

Purposes

Anti-dandruff, anti-seborrheic dermatitis

Uses

Reduces and helps eliminate scalp itching, flaking and scaling associated with dandruff and seborrheic dermatitis.

• scalp irritation and itching • flaking • scaling

Warnings

For external use only.

Ask a doctor before use if you have a condition that covers a large area of the body.

When using this product avoid contact with eyes. If contact occurs, rinse thoroughly with water.

Stop use and ask a doctor if condition worsens or does not improve after regular use of this product as directed.

Keep out of reach of children. If swallowed, get medical help or contact a Poison Control Center right away.

Directions

• shake well. • wet hair, apply shampoo and work into lather. • rinse thoroughly. • for best results, use at least twice a week or as directed by a doctor. • do not use on children under 2 years of age, except as directed by a doctor.

Other information

Store at 68-77°F (20-25°C)

Inactive ingredients

Aqua/Water/Eau, Sodium C14-16 Olefin Sulfonate, Cocamidopropyl Hydroxysultaine, Cocamidopropyl Betain, Glycol Distearate, Menthol, Cocamide MIPA, Glycerin, Melaleuca Alternifolia (Tea Tree) Leaf Oil, Magnesium Aluminum Silicate, Chlorphenesin, Guar Hydroxypropyltrimonium Chloride, Sodium Chloride, Isopropanolamine, Sodium Polynaphthalenesulfonate, Xanthan Gum, Magnesium Nitrate, Methylchloroisothiazolinone, Magnesium Chloride, Methylisothiazolinone, Phenoxyethanol, Sodium Hydroxide, Citric Acid, Parfum/Fragrance, Citronellol, Coumarin, Geraniol, Hexyl Cinnamal, Hydroxycitronellal, Limonene, Linalool, Linalyl Acetate, Terpineol

Questions? Call 1-888-398-1382

email info@denorex.com or visit www.denorex.com

ADVANCED RELIEF

Denorex®

SEVERE FLAKES

MEDICATED ANTI-DANDRUFF

SHAMPOO + CONDITIONER

DISTRIBUTED BY NEOTERIC COSMETICS, INC.

NEW YORK, NY 10003 / MADE IN CANADA

PACKAGE LABEL

NEW! 2X FLAKE FIGHTING POWER**

ADVANCED RELIEF

Denorex®

SEVERE FLAKES

MEDICATED

ANTI-DANDRUFF

SHAMPOO + CONDITIONER

PYRITHIONE ZINC 2% / DANDRUFF + SEBORRHEIC DERMATITIS

INSTANT FLAKE CONTROL

CONTROLS & RELIEVES:

√ SEVERE FLAKES

√ SCALING

√ ITCHING

√ IRRITATION

associated with dandruff + seborrheic dermatitis

2% PYRITHIONE ZINC

10 FL. OZ. (296 ml)